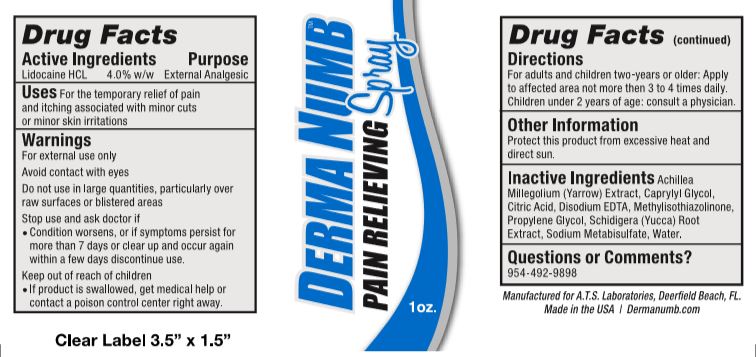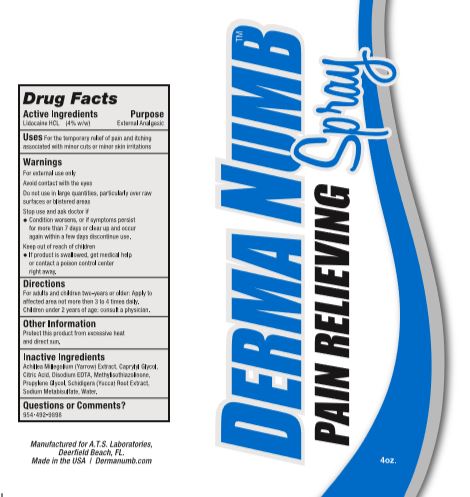 DRUG LABEL: Derma Numb Pain Relief
NDC: 70188-005 | Form: GEL
Manufacturer: A.T.S. Laboratories, LLC
Category: otc | Type: HUMAN OTC DRUG LABEL
Date: 20251111

ACTIVE INGREDIENTS: LIDOCAINE HYDROCHLORIDE 40 mg/1 g
INACTIVE INGREDIENTS: WATER; PROPYLENE GLYCOL; ACHILLEA MILLEFOLIUM; YUCCA SCHIDIGERA; CITRIC ACID MONOHYDRATE; SODIUM METABISULFITE; CAPRYLYL GLYCOL; EDETATE DISODIUM; METHYLISOTHIAZOLINONE

Derma Numb Pain Relieving Spray

Active Ingredients

Lidocaine HCL 4.0% w/w

Purpose

External Analgesic

Uses

For temporary relief of pain and itching associated with minor cuts or minor skin irritations.

Warnings

For external use only

Avoid contact with eyes

DO NOT USE

Do not usein large quantities, particularly over raw surfaces or blistered areas

Stop use and ask doctor if

• Condition worsens, or if symptoms persist for more then 7 days or clear up and occur again with a few days. Discontinue use.

Keep out of reach of children

• If product is swallowed, get medical help or contact a poison control center right away.

Directions

For adults and children two-years or older: Apply to affected area not more than 3 to 4 times daily. Children under 2 years of age: consult a physician.

Inactive Ingredients

Achillea Millegolium (Yarrow) Extract, Caprylyl Glycol, Citric Acid, Disodium EDTA, Methylisothiazolinone, Propylene Glycol, Schidigera (Yucca) Root Extract, Sodium Metabisulfate, Water.

Other Information

Protect this product from excessive heat and direct sun.

Questions or Comments?

954-492-9898